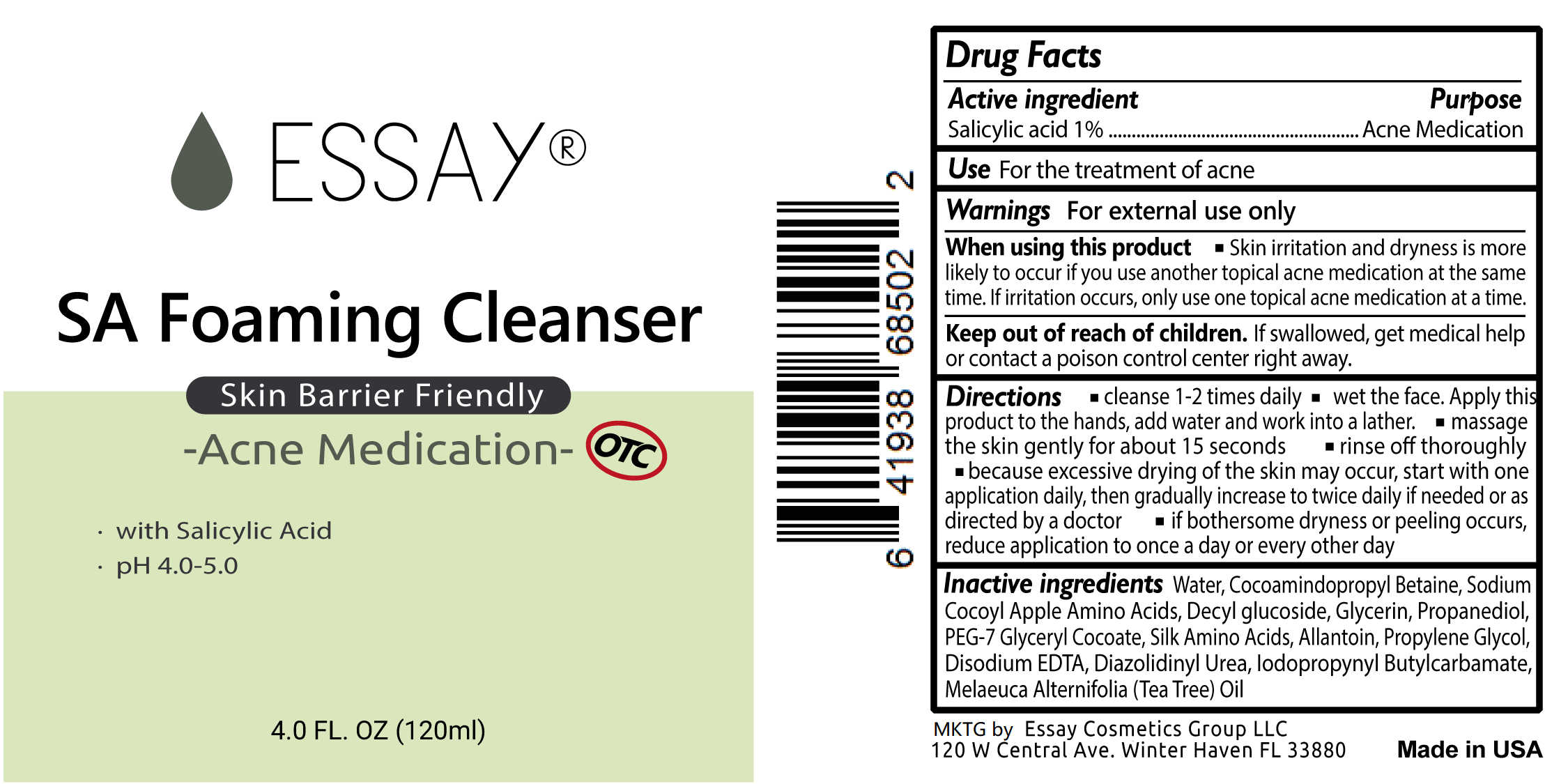 DRUG LABEL: SA Foaming Cleanser
NDC: 72900-022 | Form: SOAP
Manufacturer: Essay Cosmetics Group LLC
Category: otc | Type: HUMAN OTC DRUG LABEL
Date: 20190403

ACTIVE INGREDIENTS: SALICYLIC ACID 1.2 g/1.2 g
INACTIVE INGREDIENTS: PROPANEDIOL; DIAZOLIDINYL UREA; EDETATE DISODIUM ANHYDROUS; COCAMIDOPROPYL BETAINE; DECYL GLUCOSIDE; GLYCERIN; PEG-7 GLYCERYL COCOATE; SODIUM COCOYL APPLE AMINO ACIDS; AMINO ACIDS, SILK; ALLANTOIN; SODIUM HYDROXIDE; IODOPROPYNYL BUTYLCARBAMATE; TEA TREE OIL; WATER

SA Foaming Cleanser-Essay

Active Ingredient

1% Salicylic Acid

Product Purpose

Acne Medication

Product Use

USE For acne control and treatment

Directions

Directions [bullet] cleanse 1-2 time daily. [bullet] wet the face. Apply this product to the hands, add water and work into a lather. [bullet] massage the skin gently for about 15 seconds. [bullet] rinse off thoroughly. [bullet] because excessive drying of the skin may occur, start with one application daily, then gradually increase to twice daily if needed or as directed by a doctor [bullet] if bothersome dryness or peeling occurs, reduce application to once a day or every other day.

Inactive ingredients

Inactive ingredients Water, Cocoamindopropyl Betaine, Sodium Cocoyl Apple Amino Acid, Decyl glucoside, Glycerin, Salicylic Acid, PEG-7 Glyceryl Cocoate, Propanediol, Sodium Hydroxide, Xanthan Gum, Allantoin, Propylene Glycol, Sodium EDTA, Melaeuca Alternifolia (Tea Tree) Oil, Diazolidinyl Urea, Iodopropynyl Butylcarbamate

KEEP OUT OF REACH OF CHILDREN

If swallowed, get medical help or contact a Poison Control Center immediately.

Directions

● cleanse 1-2 time a daily

● wet the face. Apply this product to the hands, add water and work into a lather.

● massage the skin gently for about 15 seconds

● rinse off thoroughly
● because excessive drying of the skin may occur, start with one application daily, then gradually increase to two or three times daily if needed or as directed by a doctor
● if bothersome dryness or peeling occurs, reduce application to once a day or every other day.

WARNINGS

Warnings: ■ for external use only ■ when using this product, skin irritation and dryness is more likely to occur if you use another topical acne mediation at the same time. If irritation occurs, only use one topical acne medication at a time.

Principal Display Panel

SA_Foaming_Cleanser_RF.jpg